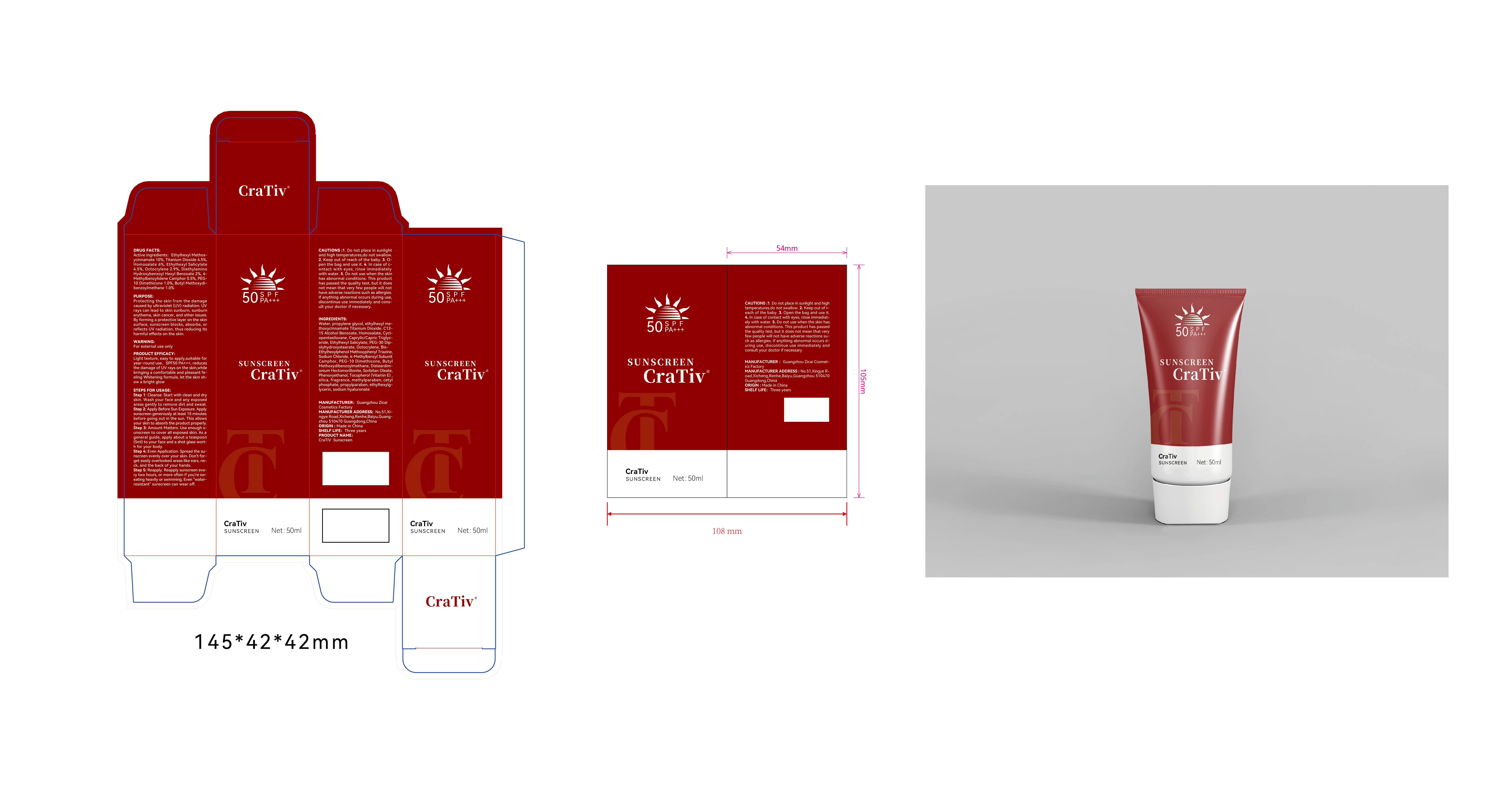 DRUG LABEL: CraTiv Sunscreen
NDC: 84301-001 | Form: LOTION
Manufacturer: Foshan Xinhai Jiayu Import and Export Trade Co., Ltd
Category: otc | Type: HUMAN OTC DRUG LABEL
Date: 20240511

ACTIVE INGREDIENTS: OCTOCRYLENE 2.9 g/100 mL; BEMOTRIZINOL 2 g/100 mL; AVOBENZONE 1 g/100 mL; HOMOSALATE 6 g/100 mL; TITANIUM DIOXIDE 4.5 g/100 mL; OCTINOXATE 10 g/100 mL; OCTISALATE 4.5 g/100 mL; ENZACAMENE 0.5 g/100 mL; DIMETHICONE 1 g/100 mL
INACTIVE INGREDIENTS: MONTMORILLONITE; CETYL PHOSPHATE; SODIUM CHLORIDE; METHYLPARABEN; PROPYLPARABEN; HYALURONATE SODIUM; MEDIUM-CHAIN TRIGLYCERIDES; CYCLOMETHICONE 5; SILICON DIOXIDE; WATER; ALKYL (C12-15) BENZOATE; SORBITAN MONOOLEATE; .ALPHA.-TOCOPHEROL; ETHYLHEXYLGLYCERIN; PROPYLENE GLYCOL; PEG-30 DIPOLYHYDROXYSTEARATE; PHENOXYETHANOL

CraTiv Sunscreen

ACTIVE INGREDIENT

Ethylhexyl methoxycinnamate 10%
Titanium dioxide 4.5%
Homosalate 6%
Ethylhexyl salicylate 4.5%
Octocrylene 2.9%
Bis-ethylhexyloxyphenolmethoxyphenyltriazine 2%
4-methylbenzylidene camphor 0.5%
DIMETHICONE 1%
Butyl methoxydibenzoylmethane 1%

PURPOSE

Protecting the skin from the damagecaused by ultraviolet (UV) radiation. UVrays can lead to skin sunburn, sunburnerythema, skin cancer, and other issuesBy forming a protective layer on the skinsurface, sunscreen blocks, absorbs,orreflects UV radiation, thus reducing itsharmful effects on the skin.

INDICATIONS AND USAGE

Protecting the skin from the damagecaused by ultraviolet (UV) radiation. UVrays can lead to skin sunburn, sunburnerythema, skin cancer, and other issuesBy forming a protective layer on the skinsurface, sunscreen blocks, absorbs,orreflects UV radiation, thus reducing itsharmful effects on the skin.

WARNINGS

For external use only

DO NOT USE

5. Do not use when the skinhas abnormal conditions. This producthas passed the quality test, but it doesnot mean that very few people will nothave adverse reactions such as allergies.lf anything abnormal occurs during usediscontinue use immediately and cons-ult your doctor if necessary

WHEN USING

1. Do not place in sunlightand high temperatures,do not swallow.2. Keep out of reach of the baby. 3. O-pen the bag and use it. 4. In case of c-ontact with eyes, rinse immediatelywith water.

STOP USE

5. Do not use when the skinhas abnormal conditions. This producthas passed the quality test, but it doesnot mean that very few people will nothave adverse reactions such as allergies.lf anything abnormal occurs during usediscontinue use immediately and cons-ult your doctor if necessary

Keep out of reach of the baby.

DOSAGE AND ADMINISTRATION

Step 1: Cleanse. Start with clean and dryskin. Wash your face and any exposedareas gently to remove dirt and sweat.
Step 2: Apply Before Sun Exposure. Applysunscreen generously at least 15 minutesbefore going out in the sun. This allowsyour skin to absorb the product properly.
Step 3: Amount Matters. Use enough s-unscreen to cover all exposed skin. As ageneral guide, apply about a teaspoon(5ml) to your face and a shot glass wort-h for your body.
Step 4: Even Application. Spread the su-nscreen evenly over your skin. Don't for-get easily overlooked areas like ears, ne-ck, and the back of your hands.
Step 5: Reapply. Reapply sunscreen eve-ry two hours, or more often if you're sw-eating heavily or swimming. Even water-resistant' sunscreen can wear off.

STORAGE AND HANDLING

1. Do not place in sunlightand high temperatures,do not swallow.2. Keep out of reach of the baby.

INACTIVE INGREDIENT

water
propylene glycol
C12-15 Alcohol Benzoate
cyclopentasiloxane
Caprylic/capric triglyceride
PEG-30 Dipolyhydroxystearate
Sodium chloride
MONTMORILLONITE
Sorbitan oleate
Phenoxyethanol
.ALPHA.-TOCOPHEROL
SILICON DIOXIDE
Methylparaben
CETYL PHOSPHATE
Propylparaben
Ethylhexylglycerin
Sodium hyaluronate